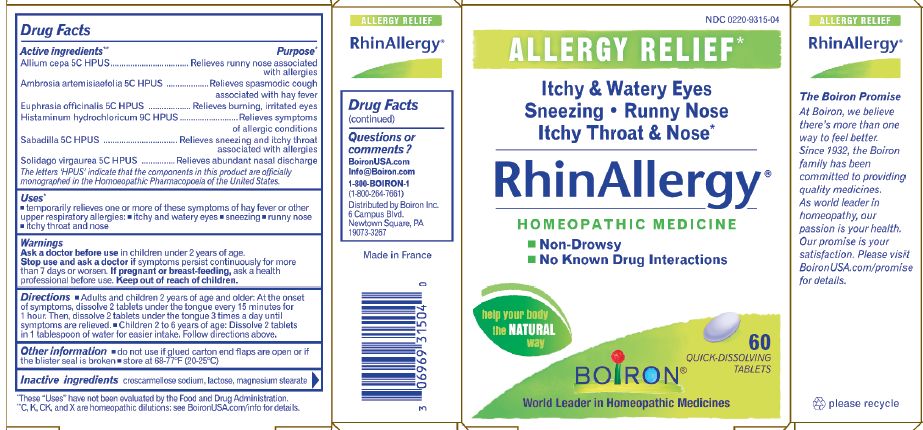 DRUG LABEL: RhinAllergy
NDC: 0220-9315 | Form: TABLET
Manufacturer: Boiron
Category: homeopathic | Type: HUMAN OTC DRUG LABEL
Date: 20200225

ACTIVE INGREDIENTS: AMBROSIA ARTEMISIIFOLIA 5 [hp_C]/1 1; SCHOENOCAULON OFFICINALE SEED 5 [hp_C]/1 1; EUPHRASIA STRICTA 5 [hp_C]/1 1; ONION 5 [hp_C]/1 1; SOLIDAGO VIRGAUREA FLOWERING TOP 5 [hp_C]/1 1; HISTAMINE DIHYDROCHLORIDE 9 [hp_C]/1 1
INACTIVE INGREDIENTS: LACTOSE, UNSPECIFIED FORM; MAGNESIUM STEARATE; CROSCARMELLOSE SODIUM

RhinAllergy Tablets

ACTIVE INGREDIENT

Allium cepa 5C HPUS

Ambrosia artemisiaefolia 5C HPUS

Euphrasia officinalis 5C HPUS

Histaminum hydrochloricum 9C HPUS

Sabadilla 5C HPUS

Solidago virgaurea 5C HPUS

PURPOSE

Allium cepa 5C HPUS....relieves runny nose associated with allergies

Ambrosia artemisiaefolia 5C HPUS ...relieves spasmodic cough associated with hay fever

Euphrasia officinalis 5C HPUS ...relieves burning, irritated eyes

Histaminum hydrochloricum 9C HPUS ...relieves symptoms of allergic conditions

Sabadilla 5C HPUS ...relieves sneezing and itchy throat associated with allergies

Solidago virgaurea 5C HPUS ...relieves abundant nasal discharge

INDICATIONS AND USAGE

temporarily relieves one or more of these symptoms of hay fever or other upper respiratory allergies, itchy and watery eyes, sneezing, runny nose, itchy throat and nose

INACTIVE INGREDIENT

magnesium stearate, lactose, croscarmellose sodium

HOW SUPPLIED

60 tablets

STORAGE AND HANDLING

store at 68-77F (20-25C)

QUESTIONS

BoironUsa.com

Info@boironusa.com

1-800-BOIRON-1

1-800-264-7661

Distributed by Boiron:

6 Campus Blvd

Newtown Square, PA 19073-3267

ask a doctor before use in children under 2 years of age

stop use and ask a doctor if symptoms persist continuously for more than 7 days or worsen

PREGNANCY OR BREAST FEEDING

if pregnant or breast-feeding, ask a health professional before use

DOSAGE AND ADMINISTRATION

Adults and children 2 years of age and older: at the onset of symptoms, dissolve 2 tablets under the tongue every 15 minutes for 1 hour, then, dissolve 2 tablets under the tongue 3 times a day until symptoms are relieved.

Children 2 to 6 years of age: Dissolve 2 tablets in 1 tablespoon of water for easier intake. Follow directions above.